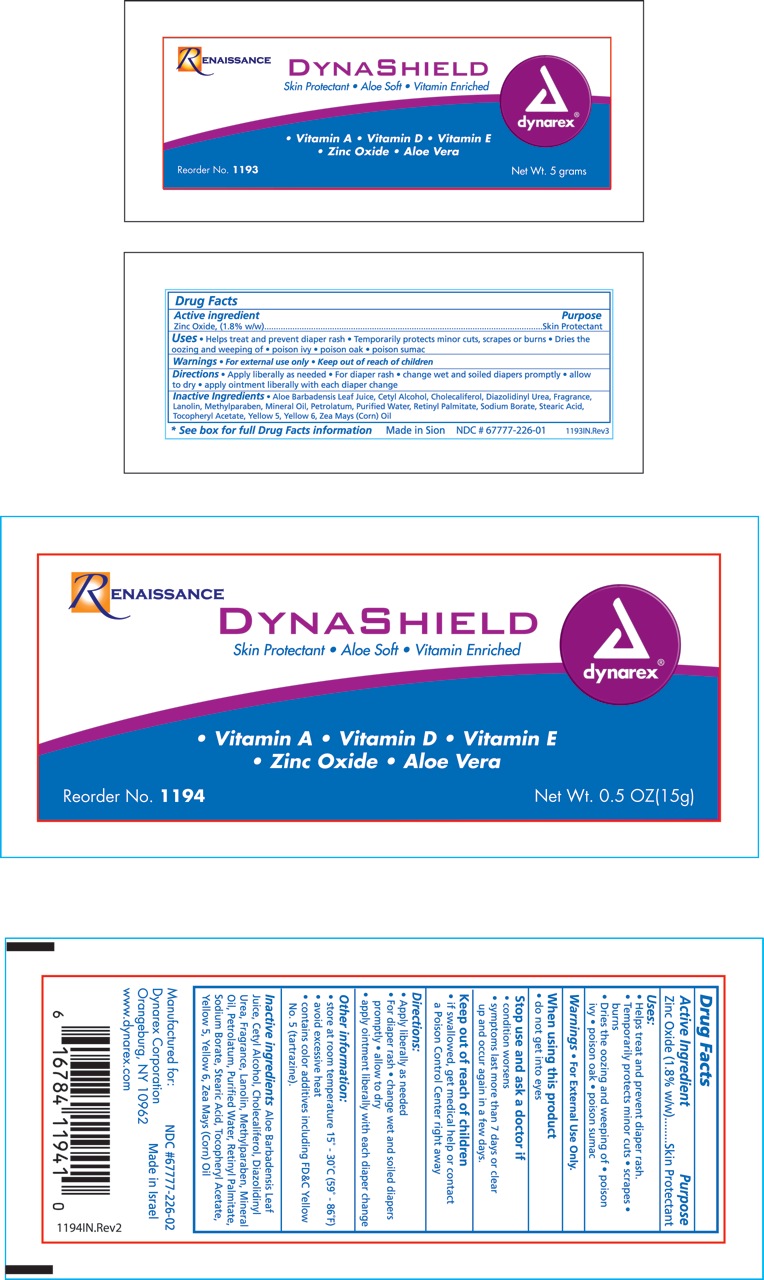 DRUG LABEL: zinc oxide
NDC: 68786-226 | Form: OINTMENT
Manufacturer: Sion Biotext Medical Ltd
Category: otc | Type: HUMAN OTC DRUG LABEL
Date: 20100122

ACTIVE INGREDIENTS: ZINC OXIDE 1.8 g/100 g
INACTIVE INGREDIENTS: ALOE VERA LEAF; CETYL ALCOHOL; DIAZOLIDINYLUREA; LANOLIN; METHYLPARABEN; MINERAL OIL; PETROLATUM; VITAMIN A PALMITATE; SODIUM BORATE; STEARIC ACID; .ALPHA.-TOCOPHEROL ACETATE, D-; CORN OIL; WATER; FD&C YELLOW NO. 5

Zinc Oxide Ointment

Active Ingredient Purpose

Zinc Oxide (1.8% w/w) Skin Protectant

Uses:

- Helps treat and prevent diaper rash
- Temporarily protects
- minor cuts
- scrapes and
- burns
- dries the oozing and weeping of
- poison ivy
- poison oak
- poison sumac

Warnings:

For External Use Only.

When using this product:

Do not get in eyes.

Stop use and ask a doctor if:

- condition worsens
- symptoms last more than 7 days or clear up and occur again in a few days, consult a physician

Keep out of reach of children.

If swallowed, get medical help or contact a Poison Control Center right away.

Directions:

For skin protectant:

- Apply liberally as needed

For diaper Rash:

- change wet and soiled diapers promptly
- allow to dry
- apply ointment liberally with each diaper change

Other information:

- Store at room temperature
- avoid excessive heat
- contains color additives including FDC yellow # 5

Principal Display Panel

Zinc Oxide Ointment